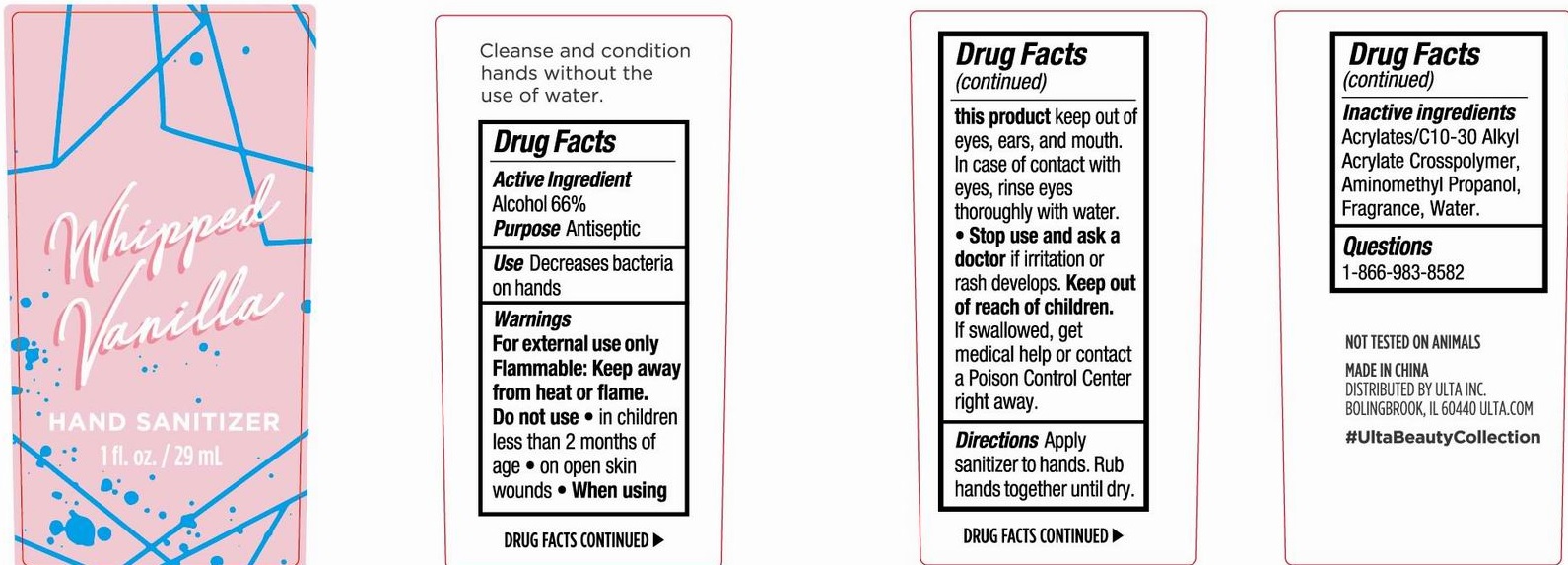 DRUG LABEL: Whipped Vanilla Hand Sanitizer
NDC: 56136-342 | Form: GEL
Manufacturer: Ganzhou Olivee Cosmetic Co., Ltd.
Category: otc | Type: HUMAN OTC DRUG LABEL
Date: 20200627

ACTIVE INGREDIENTS: ALCOHOL 66 mL/100 mL
INACTIVE INGREDIENTS: WATER; CARBOMER COPOLYMER TYPE A; AMINOMETHYLPROPANOL

HAND SANITIZER

Active ingredient

Alcohol 66%

Purpose

Antiseptic

Use

Decreases bacteria on hands

Warnings

For external use only.

Flammable. Keep product away from heat or flame.

Do not use: in children less than 2 months of age. On open skin wounds

When using this product Keep out of eyes, ears, and mouth. In case of contact with eyes, rinse eyes thoroughly with water.

Stop use and ask a doctor if irritation or rash develops.

Questions:

1-866-983-8582

Keep out of reach of children.

If swallowed, get medical help or contact a Poison Control Center right away.

Directions

Apply sanitizer to hands. Rub hands together until dry.

Inactive ingredients

Acrylates/C10-30 Alkyl Acrylate Crosspolymer, Aminomethyl Propanol, Fragrance, Water.